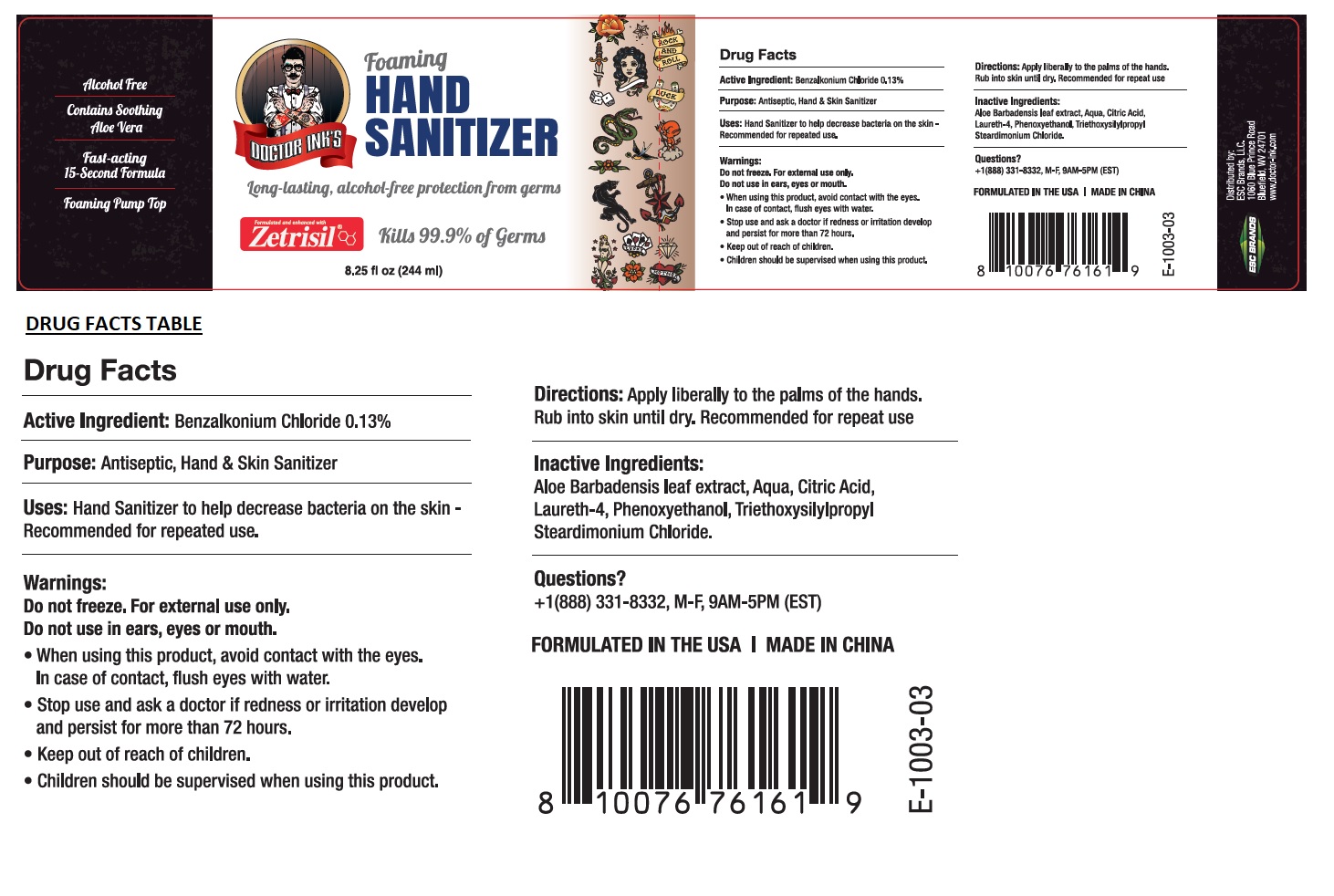 DRUG LABEL: DOCTOR INKS HAND SANITIZER
NDC: 71884-201 | Form: LIQUID
Manufacturer: Enviro Specialty Chemicals Inc
Category: otc | Type: HUMAN OTC DRUG LABEL
Date: 20241223

ACTIVE INGREDIENTS: BENZALKONIUM CHLORIDE 1.3 mg/1 mL
INACTIVE INGREDIENTS: ALOE VERA LEAF; WATER; LAURETH-4; CITRIC ACID MONOHYDRATE; PHENOXYETHANOL; TRIETHOXYSILYLPROPYL STEARDIMONIUM CHLORIDE

DOCTOR INK'S HAND SANITIZER

Active Ingredient:

Benzalkonium Chloride 0.13%

Purpose:

Antiseptic, Hand & Skin Sanitizer

Uses:

Hand Sanitizer to help decrease bacteria on the skin - Recommended for repeated use.

Warnings:

Do not freeze. For external use only. Do not use in ears, eyes or mouth.

- When using this product, avoid contact with the eyes. In case of contact, flush eyes with water.
- Stop use and ask a doctor if redness or irritation develop and persist for more than 72 hours.

- Keep out of reach of children.
- Children should be supervised when using this product.

Directions:

Apply liberally to the palms of the hands. Rub into skin until dry. Recommended for repeat use.

Inactive Ingredients:

Aloe Barbadensis leaf extract, Aqua, Citric Acid, Laureth-4, Phenoxyethanol, Triethoxysilylpropyl Steardimonium chloride.

Questions?

+1(888) 331-8332, M-F, 9AM-5PM (EST)

Long-lasting, alcohol-free protection from germs

Formulated and enhanced with Zetrisil®

Kills 99.9% of Germs

Alcohol Free

Contains Soothing Aloe Vera

Fast-acting
15-Second Formula

Foaming Pump Top

Distributed by:
ESC Brands, LLC.
1060 Blue Prince Road
Bluefield, WV 24701
www.doctor-ink.com

FORMULATED IN THE USA

MADE IN CHINA